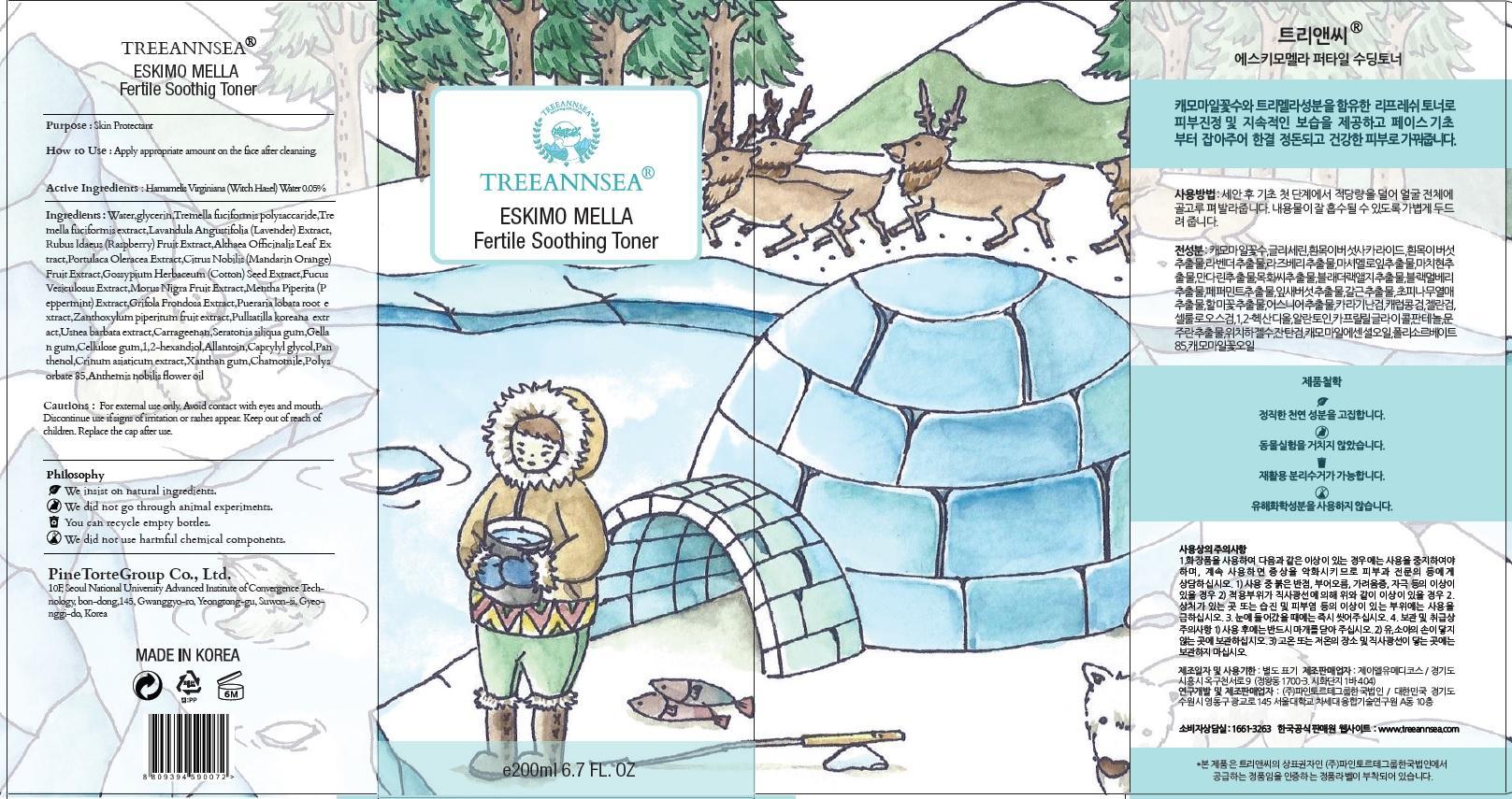 DRUG LABEL: TREEANNSEA ESKIMO MELLA FERTILE SOOTHING TONER
NDC: 69515-030 | Form: CREAM
Manufacturer: PINE TORTE GROUP CO., LTD.
Category: otc | Type: HUMAN OTC DRUG LABEL
Date: 20150318

ACTIVE INGREDIENTS: Witch Hazel 0.1 mg/200 mL
INACTIVE INGREDIENTS: Water; Glycerin

ACTIVE INGREDIENT

Active Ingredients: Hamamelis Virginiana (Witch Hazel) Water 0.05%

INACTIVE INGREDIENT

Inactive Ingredients: Water, Glycerin, Tremella fuciformis polysaccaride, Tremella fuciformis extract, Lavandula Angustifolia (Lavender) Extract, Rubus Idaeus (Raspberry) Fruit Extract, Althaea Officinalis Leaf Extract, Portulaca Oleracea Extract, Citrus Nobilis (Mandarin Orange) Fruit Extract, Gossypium Herbaceum (Cotton) Seed Extract, Fucus Vesiculosus Extract, Morus Nigra Fruit Extract, Mentha Piperita (Peppermint) Extract, Grifola Frondosa Extract, Pueraria lobata root extract, Zanthoxylum piperitum fruit extract/Pullsatilla koreana extract, Usnea barbata extract, Carrageenan, Seratonia siliqua gum, Gellan gum, Cellulose gum, 1,2-hexandiol, Allantoin, Caprylyl glycol, Panthenol, Crinum asiaticum extract, Xanthan gum, Chamomile, Polysorbate 85, Anthemis nobilis flower oil

PURPOSE

Purpose: Skin Protectant

Cautions

Cautions: For external use only. Avoid contact with eyes and mouth. Discountinue use if signs of irritation or rashes appear. Keep out of reach of children. Replace the cap after use.

KEEP OUT OF REACH OF CHILDREN

INDICATIONS & USAGE

How to use: Apply appropriate amount on the face after cleansing.

DOSAGE & ADMINISTRATION

How to use: Apply appropriate amount on the face after cleansing.